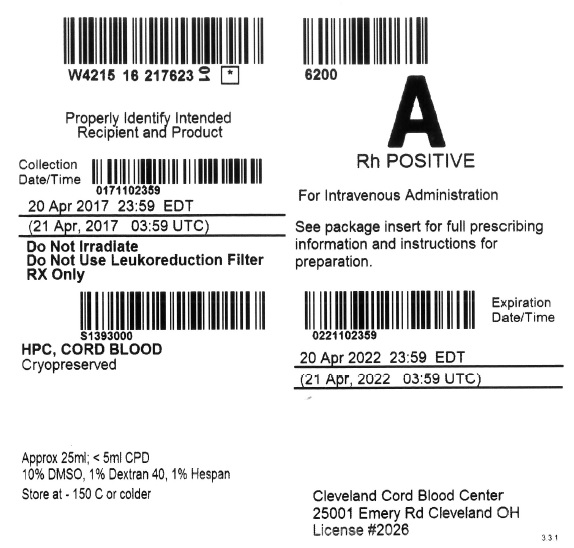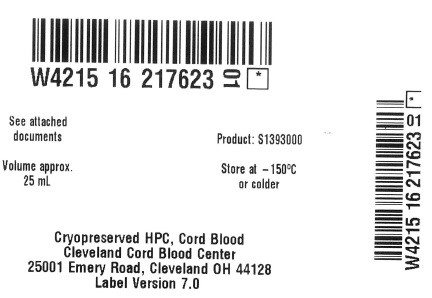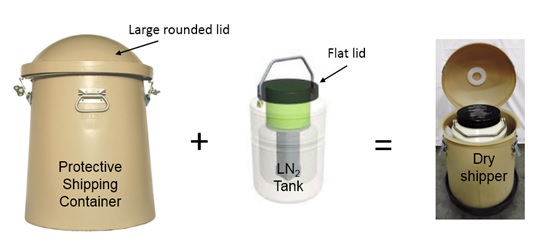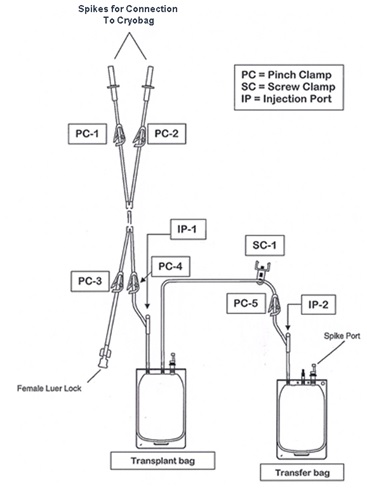 DRUG LABEL: CLEVECORD
NDC: W4215-S1393 | Form: INJECTION, SUSPENSION
Manufacturer: Cleveland Cord Blood Center
Category: other | Type: LICENSED MINIMALLY MANIPULATED CELLS LABEL
Date: 20170425

ACTIVE INGREDIENTS: human cord blood hematopoietic progenitor cell 500000000 1/25 mL
INACTIVE INGREDIENTS: DIMETHYL SULFOXIDE; HYDROXYETHYL STARCH 130/0.4; DEXTRAN 40

HIGHLIGHTS OF PRESCRIBING INFORMATION

These highlights do not include all the information needed to use CLEVECORD safely and effectively. See full prescribing information for CLEVECORD.
CLEVECORD (HPC, Cord Blood)
Injectable Suspension for Intravenous Use
Initial U.S. Approval: 1 September 2016

WARNING: FATAL INFUSION REACTIONS, GRAFT VERSUS HOST DISEASE, ENGRAFTMENT SYNDROME, AND GRAFT FAILURE

See full prescribing information for complete boxed warning.

- Fatal infusion reactions: Monitor patients during infusion and discontinue for severe reactions. (5.1, 5.2)
- Graft-versus-host disease (GVHD): GVHD may be fatal. Administration of immunosuppressive therapy may decrease the risk of GVHD. (5.3)
- Engraftment syndrome: Engraftment syndrome may be fatal. Treat engraftment syndrome promptly with corticosteroids. (5.4)
- Graft failure: Graft failure may be fatal. Monitor patients for laboratory evidence of hematopoietic recovery. (5.5)

1 INDICATIONS AND USAGE

CLEVECORD, HPC (Hematopoietic Progenitor Cell), Cord Blood, is an allogeneic cord blood hematopoietic progenitor cell therapy indicated for use in unrelated donor hematopoietic progenitor cell transplantation procedures in conjunction with an appropriate preparative regimen for hematopoietic and immunologic reconstitution in patients with disorders affecting the hematopoietic system that are inherited, acquired, or result from myeloablative treatment. (1)

The risk benefit assessment for an individual patient depends on the patient characteristics, including disease, stage, risk factors, and specific manifestations of the disease, on characteristics of the graft, and on other available treatments or types of hematopoietic progenitor cells. (1)

2 DOSAGE AND ADMINISTRATION

- For intravenous use only.
- Do not irradiate.
- Unit selection and administration of CLEVECORD should be done under the direction of a physician experienced in hematopoietic progenitor cell transplantation. (2)
- The recommended minimum dose is 2.5 x 10^7 nucleated cells/kg at cryopreservation. (2.1)
- Do not administer CLEVECORD through the same tubing with other products except for normal saline. (2.3)

3 DOSAGE FORMS AND STRENGTHS

Each unit contains a minimum of 5 x 10^8 total nucleated cells with at least 1.25 x 10^6 viable CD34+ cells at the time of cryopreservation. The exact pre-cryopreservation nucleated cell content of each unit is provided in the accompanying records. (3)

4 CONTRAINDICATIONS

None.

5 WARNINGS AND PRECAUTIONS

- Hypersensitivity Reactions (5.1)
- Infusion Reactions (5.2)
- Graft-versus-Host Disease (5.3)
- Engraftment Syndrome (5.4)
- Graft Failure (5.5)
- Malignancies of Donor Origin (5.6)
- Transmission of Serious Infections (5.7)
- Transmission of Rare Genetic Diseases (5.8)

6 ADVERSE REACTIONS

Mortality, from all causes, at 100 days post-transplant was 25%. (5, 6.1)

The most common infusion-related adverse reactions (≥5%) are hypertension, vomiting, nausea, bradycardia, and fever. (6.1)

To report SUSPECTED ADVERSE REACTIONS, contact the Cleveland Cord Blood Center at 1-216-378-3032 or FDA at 1-800-FDA-1088 or www.fda.gov/medwatch.

FULL PRESCRIBING INFORMATION

WARNING: FATAL INFUSION REACTIONS, GRAFT VERSUS HOST DISEASE, ENGRAFTMENT SYNDROME, AND GRAFT FAILURE

Fatal infusion reactions: CLEVECORD administration can result in serious, including fatal, infusion reactions. Monitor patients and discontinue CLEVECORD infusion for severe reactions. [See Warnings and Precautions (5.1, 5.2)]

Graft-versus-host disease (GVHD): GVHD is expected after administration of CLEVECORD and may be fatal. Administration of immunosuppressive therapy may decrease the risk of GVHD. [See Warnings and Precautions (5.3)]

Engraftment syndrome: Engraftment syndrome may progress to multiorgan failure and death. Treat engraftment syndrome promptly with corticosteroids. [See Warnings and Precautions (5.4)]

Graft failure: Graft failure may be fatal. Monitor patients for laboratory evidence of hematopoietic recovery. Prior to choosing a specific unit of CLEVECORD, consider testing for HLA antibodies to identify patients who are alloimmunized. [See Warnings and Precautions (5.5)]

1 INDICATIONS AND USAGE

CLEVECORD, HPC (Hematopoietic Progenitor Cell), Cord Blood, is an allogeneic cord blood hematopoietic progenitor cell therapy indicated for use in unrelated donor hematopoietic progenitor stem cell transplantation procedures in conjunction with an appropriate preparative regimen for hematopoietic and immunologic reconstitution in patients with disorders affecting the hematopoietic system that are inherited, acquired, or result from myeloablative treatment.

The risk benefit assessment for an individual patient depends on the patient characteristics, including disease, stage, risk factors, and specific manifestations of the disease, on characteristics of the graft, and on other available treatments or types of hematopoietic progenitor cells.

2 DOSAGE AND ADMINISTRATION

- For intravenous use only.
- Do not irradiate.

Unit selection and administration of CLEVECORD should be done under the direction of a physician experienced in hematopoietic progenitor cell transplantation.

2.1 Dosing

The recommended minimum dose is 2.5 x 10^7 nucleated cells/kg at cryopreservation. Multiple units may be required in order to achieve the appropriate dose.

Matching for at least 4 of 6 HLA-A antigens, HLA-B antigens, and HLA-DRB1 alleles is recommended. The HLA typing and nucleated cell content for each individual unit of CLEVECORD are documented in the accompanying records.

2.2 Preparation for Infusion

CLEVECORD should be prepared by a trained healthcare professional.

- Do not irradiate CLEVECORD.
- See the appended detailed instructions for preparation of CLEVECORD for infusion.
- CLEVECORD may be stored at 15-25°C for up to 4 hours from time of thaw. [See Instructions for Preparation for Infusion]
- The recommended limit on DMSO administration is 1 gram per kg body weight per day. [See Warnings and Precautions (5.2) and Overdosage (10)]

2.3 Administration

CLEVECORD should be administered under the supervision of a qualified healthcare professional experienced in hematopoietic progenitor cell transplantation.

1. Confirm the identity of the patient for the specified unit of CLEVECORD prior to administration.
2. Confirm that emergency medications are available for use in the immediate area.
3. Ensure the patient is hydrated adequately.
4. Pre-medicate the patient 30 to 60 minutes before the administration of CLEVECORD. Premedication should include any or all of the following: antipyretics, histamine antagonists, and corticosteroids.
5. Inspect the product for any abnormalities, such as unusual particulates, and for breaches of container integrity prior to administration. Prior to infusion, discuss all such product irregularities with the laboratory issuing the product for infusion.
6. Administer CLEVECORD by intravenous infusion. Do not administer in the same tubing concurrently with products other than 0.9% Sodium Chloride, Injection (USP). CLEVECORD may be infused through a 170 to 260 micron filter designed to remove clots. Do NOT use a filter designed to remove leukocytes.
7. Infuse CLEVECORD over 15 to 60 minutes depending on the volume of the product and the weight of the patient. The rate of infusion should not exceed a maximum of 5 milliliters per kilogram per hour. Reduce the infusion rate if the patient cannot tolerate the fluid load. Discontinue the infusion in the event of an allergic reaction or if the patient develops a moderate to severe infusion reaction. [See Warnings and Precautions (5.2) and Adverse Reactions (6.1)]
8. Monitor the patient for adverse reactions during, and for at least six hours after, administration. Because CLEVECORD contains lysed red cells that may cause renal failure, careful monitoring of urine output is also recommended.

NOTE: If product is being prepared for a multi-unit infusion, prepare and infuse each unit independently. Should a reaction occur, appropriately manage the reaction before another unit is thawed for infusion

3 DOSAGE FORMS AND STRENGTHS

Each CLEVECORD unit contains a minimum of 5 x 10^8 total nucleated cells with a minimum of 1.25 x 10^6 viable CD34+ cells, suspended in 10% dimethyl sulfoxide (DMSO) and 1% Dextran 40, at the time of cryopreservation.

The exact pre-cryopreservation nucleated cell content is provided in the accompanying records.

4 CONTRAINDICATIONS

None.

5 WARNINGS AND PRECAUTIONS

5.1 Hypersensitivity Reactions

Allergic reactions may occur with infusion of HPC, Cord Blood, including CLEVECORD. Reactions include bronchospasm, wheezing, angioedema, pruritus, and hives [see Adverse Reactions (6.1)]. Serious hypersensitivity reactions, including anaphylaxis, also have been reported. These reactions may be due to dimethyl sulfoxide (DMSO), Dextran 40, hydroxyethyl starch, or a plasma component of CLEVECORD.

CLEVECORD may contain residual antibiotics if the cord blood donor was exposed to antibiotics in utero. Patients with a history of allergic reactions to antibiotics should be monitored for allergic reactions following CLEVECORD administration.

5.2 Infusion Reactions

Infusion reactions are expected to occur and may include nausea, vomiting, fever, rigors or chills, flushing, dyspnea, hypoxemia, chest tightness, hypertension, tachycardia, bradycardia, dysgeusia, hematuria, and mild headache. Premedication with antipyretics, histamine antagonists, and corticosteroids may reduce the incidence and intensity of infusion reactions.

Severe reactions, including respiratory distress, severe bronchospasm, severe bradycardia with heart block or other arrhythmias, cardiac arrest, hypotension, hemolysis, elevated liver enzymes, renal compromise, encephalopathy, loss of consciousness, and seizure also may occur. Many of these reactions are related to the amount of DMSO administered. Minimizing the amount of DMSO administered may reduce the risk of such reactions, although idiosyncratic responses may occur even at DMSO doses thought to be tolerated. The actual amount of DMSO depends on the method of preparation of the product for infusion. Limiting the amount of DMSO infused to no more than 1 gram per kilogram per day is recommended. [See Overdosage (10)]

Infusion reactions may begin within minutes of the start of infusion of CLEVECORD, although symptoms may continue to intensify and not peak for several hours after completion of the infusion. Monitor the patient closely during this period. When a reaction occurs, discontinue the infusion and institute supportive care as needed. If infusing more than one unit of HPC, Cord Blood on the same day, do not administer subsequent units until all signs and symptoms of infusion reactions from the prior unit have resolved.

5.3 Graft-versus-Host Disease

Acute and chronic graft-versus-host disease (GVHD) may occur in patients who have received CLEVECORD. Classic acute GVHD is manifested as fever, rash, elevated bilirubin and liver enzymes, and diarrhea. Patients transplanted with CLEVECORD should receive immunosuppressive drugs to decrease the risk of GVHD. [See Adverse Reactions (6.1)]

5.4 Engraftment Syndrome

Engraftment syndrome is manifested as unexplained fever and rash in the peri-engraftment period. Patients with engraftment syndrome also may have unexplained weight gain, hypoxemia, and pulmonary infiltrates in the absence of fluid overload or cardiac disease. If untreated, engraftment syndrome may progress to multiorgan failure and death. Once engraftment syndrome is recognized, begin treatment with corticosteroids in order to ameliorate the symptoms. [See Adverse Reactions (6.1)]

5.5 Graft Failure

Primary graft failure, which may be fatal, is defined as failure to achieve an absolute neutrophil count greater than 500 per microliter blood by Day 42 after transplantation. Immunologic rejection is the primary cause of graft failure. Patients should be monitored for laboratory evidence of hematopoietic recovery. Consider testing for HLA antibodies in order to identify patients who are alloimmunized prior to transplantation and to assist with choosing a unit with a suitable HLA type for the individual patient. [See Adverse Reactions (6.1)]

5.6 Malignancies of Donor Origin

Patients who have undergone HPC, Cord Blood transplantation may develop post-transplant lymphoproliferative disorder (PTLD), manifested as a lymphoma-like disease favoring non- nodal sites. PTLD is usually fatal if not treated.

The incidence of PTLD appears to be higher in patients who have received antithymocyte globulin. The etiology is thought to be donor lymphoid cells transformed by Epstein-Barr virus (EBV). Serial monitoring of blood for EBV DNA may be warranted in high-risk groups.

Leukemia of donor origin also has been reported in HPC, Cord Blood recipients. The natural history is presumed to be the same as that for de novo leukemia.

5.7 Transmission of Serious Infections

Transmission of infectious disease may occur because CLEVECORD is derived from human blood. Disease may be caused by known or unknown infectious agents. Donors are screened for increased risk of infection with human immunodeficiency virus (HIV), human T-cell lymphotropic virus (HTLV), hepatitis B virus (HBV), hepatitis C virus (HCV), T. pallidum, T. cruzi, West Nile Virus (WNV), transmissible spongiform encephalopathy (TSE) agents, vaccinia, and Zika virus. Donors are also screened for clinical evidence of sepsis, and communicable disease risks associated with xenotransplantation. Maternal blood samples are tested for HIV types 1 and 2, HTLV types I and II, HBV, HCV, T. pallidum, WNV, and T. cruzi. CLEVECORD is tested for sterility. There may be an effect on the reliability of the sterility test results if the cord blood donor’s mother was treated with antibiotics. These measures do not totally eliminate the risk of transmitting these or other transmissible infectious diseases and disease agents. Report the occurrence of a transmitted infection to the Cleveland Cord Blood Center at 1-216-378-3032.

Testing is also performed for evidence of donor infection due to cytomegalovirus (CMV).

Test results may be found in the accompanying records.

5.8 Transmission of Rare Genetic Diseases

CLEVECORD may transmit rare genetic diseases involving the hematopoietic system for which donor screening and/or testing has not been performed [see Adverse Reactions (6.1)]. Cord blood donors have been screened by family history to exclude inherited disorders of the blood and marrow. CLEVECORD has been tested to exclude donors with sickle cell anemia, and anemias due to abnormalities in hemoglobins C, D, and E. Because of the age of the donor at the time CLEVECORD collection takes place, the ability to exclude rare genetic diseases is severely limited.

6 ADVERSE REACTIONS

Day-100 mortality from all causes was 25%.

The most common infusion-related adverse reactions (≥5%) are hypertension, vomiting, nausea, bradycardia, and fever.

6.1 Clinical Trials Experience

Because clinical trials are conducted under widely varying conditions, adverse reaction rates observed in the clinical trials of a drug cannot be directly compared to rates in the clinical trials of another drug and may not reflect the rates observed in practice.

The safety assessment of CLEVECORD is based primarily on review of the data submitted to the FDA dockets from various sources, the dataset from the COBLT Study, and published literature.

Infusion Reactions

The data described in Table 1 reflect exposure to 442 infusions of HPC, Cord Blood (from multiple cord blood banks) in patients treated using a total nucleated cell dose ≥2.5 x 10^7/kg on a single-arm trial or expanded access use (the COBLT Study). The population was 60% male and the median age was 5 years (range 0.05 to 68 years), and included patients treated for hematologic malignancies, inherited metabolic disorders, primary immunodeficiencies, and bone marrow failure. Preparative regimens and graft-versus-host disease prophylaxis were not standardized. The most common infusion reactions were hypertension, vomiting, nausea, and sinus bradycardia. Hypertension and any grades 3-4 infusion-related reactions occurred more frequently in patients receiving HPC, Cord Blood in volumes greater than 150 milliliters and in pediatric patients. The rate of serious adverse cardiopulmonary reactions was 0.8%.

Table 1: Incidence of Infusion-Related Adverse Reactions Occurring in ≥ 1% of Infusions (the COBLT Study)

 | Any Grade % | Grade 3-4 %
Any reaction | 65.4 % | 27.6 %
Hypertension | 48.0 % | 21.3 %
Vomiting | 14.5 % | 0.2 %
Nausea | 12.7 % | 5.7 %
Sinus bradycardia | 10.4 % | 0.0 %
Fever | 5.2 % | 0.2 %
Sinus tachycardia | 4.5 % | 0.2 %
Allergy | 3.4 % | 0.2 %
Hypotension | 2.5 % | 0.0 %
Hemogloburia | 2.1 % | 0.0 %
Hypoxia | 2.0 % | 2.0 %

Information on infusion reactions was available from voluntary reports for 91 patients who received a total nucleated cell dose of ≥ 2.5 x 10^7/kg from at least a single unit of CLEVECORD, alone or in combination with another unit of HPC, Cord Blood and who had an HLA match > 3/6. The population included 55% males and 45% females with median age of 38 years (range <1-68 years). Preparative regimens and graft-versus-host disease prophylaxis were not standardized. The reactions were not graded. An infusion reaction occurred in 20% of patients. The most common infusion reactions, occurring in ≥ 1% of infusions, were hypertension (17%), nausea or vomiting (3%), and hypoxia (3%).

Other Adverse Reactions

For other adverse reactions, the raw clinical data from the docket were pooled for 1299 (120 adult and 1179 pediatric) patients transplanted with HPC, Cord Blood (from multiple cord blood banks) with total nucleated cell dose of ≥ 2.5 x 10^7/kg. Of these, 66% (n=862) underwent transplantation as treatment for hematologic malignancy. The preparative regimens and graft-versus-host disease prophylaxis varied. The median total nucleated cell dose was 6.4 x 10^7/kg (range, 2.5-73.8 x 10^7/kg). For these patients, Day-100 mortality from all causes was 25%. Primary graft failure occurred in 16%; 42% developed grades 2-4 acute graft-versus-host disease; and 19% developed grades 3-4 acute graft-versus-host disease.

Data from the published literature and from observational registries, institutional databases, and cord blood bank reviews reported to the docket for HPC, Cord Blood (from multiple cord blood banks) revealed nine cases of donor cell leukemia, one case of transmission of infection, and one report of transplantation from a donor with an inheritable genetic disorder. The data are insufficient to support reliable estimates of the incidences of these events.

In the COBLT Study, 15% of the patients developed engraftment syndrome.

8 USE IN SPECIFIC POPULATIONS

8.1 Pregnancy

Risk Summary

There are no data with CLEVECORD use in pregnant women to inform a product-associated risk. Animal reproduction studies have not been conducted with CLEVECORD. In the U.S. general population, the estimated background risk of major birth defects and miscarriage in clinically recognized pregnancies is 2-4% and 15-20%, respectively.

8.2 Lactation

Risk Summary

There is no information regarding the presence of CLEVECORD in human milk, the effects on the breastfed infant, or the effects on milk production. The developmental and health benefits of breastfeeding should be considered along with the mother’s clinical need for CLEVECORD and any potential adverse effects on the breastfed infant from CLEVECORD or from the underlying maternal condition.

8.4 Pediatric Use

HPC, Cord Blood has been used in pediatric patients with disorders affecting the hematopoietic system that are inherited, acquired, or resulted from myeloablative treatment. [See Dosage and Administration (2), Adverse Reactions (6), and Clinical Studies (14)]

8.5 Geriatric Use

Clinical studies of HPC, Cord Blood, (from multiple cord blood banks) did not provide sufficient numbers of subjects aged 65 and over to determine whether they respond differently than younger subjects. In general, administration of CLEVECORD to patients over age 65 should be cautious, reflecting their greater frequency of decreased hepatic, renal, or cardiac function, and of concomitant disease or other drug therapy.

8.6 Renal Disease

CLEVECORD contains Dextran 40, which is eliminated by the kidneys. The safety of CLEVECORD has not been established in patients with renal insufficiency or renal failure.

10 OVERDOSAGE

10.1 Human Overdosage Experience

There has been no experience with overdose of HPC, Cord Blood in human clinical trials. Single doses of CLEVECORD up to 45 x 10^7 TNC/kg have been administered. HPC, Cord Blood prepared for infusion may contain dimethyl sulfoxide (DMSO). The maximum dose of DMSO has not been established, but it is customary not to exceed a DMSO dose of 1 gm/kg/day when given intravenously. Several cases of altered mental status and coma have been reported with higher doses of DMSO.

10.2 Management of Overdose

For DMSO overdose, general supportive care is indicated. The role of other interventions to treat DMSO overdose has not been established.

11 DESCRIPTION

CLEVECORD consists of hematopoietic progenitor cells, monocytes, lymphocytes, and granulocytes from human cord blood for intravenous infusion. Blood recovered from umbilical cord and placenta is volume reduced and partially depleted of red blood cells and plasma.

The active ingredient is hematopoietic progenitor cells which express the cell surface marker CD34. The potency of cord blood is determined by measuring the numbers of total nucleated cells (TNC) and CD34+ cells, and cell viability. Each unit of CLEVECORD contains a minimum of 5 x 10^8 total nucleated cells with at least 1.25 x 10^6 viable CD34+ cells at the time of cryopreservation. The cellular composition of CLEVECORD depends on the composition of cells in the blood recovered from the umbilical cord and placenta of the donor. The actual nucleated cell count, the CD34^+ cell count, the ABO group, and the HLA typing are listed in the accompanying records sent with each individual unit.

CLEVECORD has the following inactive ingredients: dimethyl sulfoxide (DMSO), citrate phosphate dextrose (CPD), hydroxyethyl starch, and Dextran 40. When prepared for infusion according to instructions, the infusate contains the following inactive ingredients: Dextran 40, human serum albumin, DMSO, residual hydroxyethyl starch and CPD.

12 CLINICAL PHARMACOLOGY

12.1 Mechanism of Action

Hematopoietic stem/progenitor cells from HPC, Cord Blood migrate to the bone marrow where they divide and mature. The mature cells are released into the bloodstream, where some circulate and others migrate to tissue sites, partially or fully restoring blood counts and function, including immune function, of blood-borne cells of marrow origin. [See Clinical Studies (14)]

In patients with enzymatic abnormalities due to certain severe types of storage disorders, mature leukocytes resulting from HPC, Cord Blood transplantation may synthesize enzymes that may be able to circulate and improve cellular functions of some native tissues. However, the precise mechanism of action is unknown.

14 CLINICAL STUDIES

The effectiveness of CLEVECORD as defined by hematopoietic reconstitution, was demonstrated in one single-arm prospective study and in retrospective reviews of data from an observational database for CLEVECORD and in data in the dockets and public information. Of the 1299 patients in the docket and public data, 66% (n=862) underwent transplantation as treatment for hematologic malignancy. Results for patients who received a total nucleated cell dose ≥2.5 x 10^7/kg are shown in Table 2. Neutrophil recovery is defined as the time from transplantation to an absolute neutrophil count more than 500 per microliter. Platelet recovery is the time to a platelet count more than 20,000 per microliter. Erythrocyte recovery is the time to a reticulocyte count greater than 30,000 per microliter. The total nucleated cell dose and degree of HLA match were inversely associated with the time to neutrophil recovery in the docket data.

Table 2: Hematopoietic Recovery for Patients Transplanted with HPC, Cord Blood, Total Nucleated Cell (TNC) Dose ≥ 2.5 x 10^7/kg

Data Source | COBLT Study* | Docket* and Public Data* | CLEVECORD**
Design | Single-arm prospective | Retrospective | Retrospective
Number of patients | 324 | 1299 | 91***
Median age (range) | 4.6 (0.07 – 52.2) yrs | 7.0 (<1 – 65.7) yrs | 38 (<1 – 68) yrs
Gender | 59 % male; 41 % female | 57 % male; 43 % female | 55 % male; 45 % female
Median TNC Dose (range) (x 10^7kg) | 6.7 (2.6 – 38.8) | 6.4 (2.5 – 73.8) | 4.6 (2.9 – 45.0)
Neutrophil Recovery at Day 42 (95% CI) | 76%; (71% – 81%) | 77%; (75% – 79%) | 96%; (92% - 100%)
Platelet Recovery at Day 100 (20,000/uL) (95% CI) | 57%; (51% – 63%) | - | 92%; (85% - 99%)
Platelet Recovery at Day 100 (50,000/uL) (95% CI) | 46%; (39% – 51%) | 45%; (42% – 48%) | 83%; (73% - 93%)
Erythrocyte Recovery at Day 100 (95% CI) | 65%; (58% – 71%) | - | -
Median time to Neutrophil Recovery | 27 days | 25 days | 18 days
Median time to Platelet Recovery (20,000/uL) | 90 days | - | 41 days
Median time to Platelet Recovery (50,000/uL) | 113 days | 122 days | 43 days
Median time to Erythrocyte Recovery | 64 days | - | -

* HPC, Cord Blood (from multiple cord blood banks)

**Data from patients who received a suitable allograft (i.e., TNC dose ≥ 2.5 x 10^7/kg and HLA match > 3/6) with at least a single unit of CLEVECORD.

***All 91 patients had evaluable data for age, sex, and cell dose. Since not all of the 91 patients had evaluable data for all of the listed outcomes parameters, the numbers of patients treated (N) differ for the various listed outcomes parameters. Numbers of patients treated (N) for neutrophil recovery, platelet recovery ≥ 20k, platelet recovery ≥ 50k are: 76 (excludes patients who died prior to D42 and patients with missing data), 63 (excludes patients who died prior to D100 and patients with missing data), and 53 (excludes patients who died prior to D100 and patients with missing data), respectively.

16 HOW SUPPLIED/STORAGE AND HANDLING

CLEVECORD is supplied as a cryopreserved cell suspension in a sealed bag containing a minimum of 5 x 10^8 total nucleated cells with a minimum of 1.25 x 10^6 viable CD34^+ cells in a volume of 25 milliliters (ISBT 128, Product Code S1393, ISBT 128 Facility Identifier Number W4215). The exact pre-cryopreservation nucleated cell content is provided in the accompanying records.

Store CLEVECORD at or below -150°C until ready for thawing and preparation.

17 PATIENT COUNSELING INFORMATION

Discuss the following with patients receiving CLEVECORD:

- Report immediately any signs and symptoms of acute infusion reactions, such as fever, chills, fatigue, breathing problems, dizziness, nausea, vomiting, headache, or muscle aches.
- Report immediately any signs or symptoms suggestive of graft-versus-host disease, including rash, diarrhea, or yellowing of the eyes.

INSTRUCTIONS FOR PREPARATION FOR INFUSION

I EQUIPMENT, REAGENTS, AND SUPPLIES

Equipment:

- Biological safety cabinet
- Water bath, 37°C ± 1°C
- Tube heat sealer compatible with polyvinyl chloride (PVC) plastic
- Scale
- Automated cell counter and/or microscope and cell count chamber for cell count and viability determination (optional)
- Thermogenesis canister opener
- Vapor phase liquid nitrogen (LN2) freezer at -150°C or colder or a fully charged dry shipper. (The dry shipper equipment used for shipment of CLEVECORD can be used for temporary storage of the frozen product at the Transplant Center, if a LN2 freezer or sufficient freezer space is not available.)
- Plasma extractor
- Centrifuge

Reagents:

- 5% Albumin (Human), USP
- Dextran 40 in Sodium Chloride Injection, USP

Supplies:

- Protective cryogloves
- Transplant processing two-bag set (for example, Pall Medical 791-03)
- Sterile plastic zip-lock bags
- Sterile disposable syringes: (5) 60 mL
- 18G injection needles
- 16G x 1½ injection needles
- Hemostats (optional)
- Alcohol prep pads
- Iodine swab sticks
- Sterile overwrap bag, if available

Forms:

- Dry Shipper and HPC, Cord Blood Receipt Form
- Instructions for Receipt of Dry Shipper and HPC, Cord Blood at Transplant Center

II RECEIPT INSTRUCTIONS

CLEVECORD is shipped frozen inside a steel canister placed inside a liquid nitrogen (LN2) charged tank specifically designed to keep the temperature at or below -150°C (dry shipper). Dry shippers consist of a protective shipping container with a large rounded lid, carrying a LN2 tank with a flat lid (see Figure 1). CLEVECORD must be stored at or below -150°C either in the LN2 tank inside the dry shipper for short-term storage (up to 48 hours), or inside a LN2-cooled storage device at the Transplant Center for storage greater than 48 hours. Recharge the tank with fresh LN2 if CLEVECORD is to remain stored in the dry shipper for more than 48 hours.

Figure 1: Dry shipper components and configuration

Use the following instructions to complete the “Dry Shipper and HPC, Cord Blood Receipt Form” confirming receipt of the CLEVECORD unit and verifying the identity of the unit for the intended recipient. Two trained transplant center staff members are required to receive and verify the CLEVECORD unit.

a. Inspect the dry shipper on receipt for tampering or damage.

b. Cut and remove the blue NMDP zip tie, any additional zip ties, and cellophane shipping wrap. Open the large rounded lid of the protective shipping container.

c. Inspect the temperature data logger which is located on top of the flat lid of the LN2 tank inside of the dry shipper. Observe the temperature indicated on the data logger, and in Section 2 of the Dry Shipper and HPC, Cord Blood Receipt Form record if the indicated temperature is at or below -150°C.

NOTE: After return of the dry shipper, the Cleveland Cord Blood Center will download the temperature recordings from the data logger. Upon request by the transplant center, a printout of the temperature readings will be provided by fax or email to validate that the CLEVECORD unit was maintained at or below -150°C at all times during shipment.

d. Remove the paperwork packet attached to the inside of the large rounded lid. Obtain the padlock combination enclosed in the packet. Use the padlock combination to remove the padlock from the flat lid on the LN2 tank inside of the dry shipper.

e. Carefully remove the lid from the LN2 tank by slight rotation and, using cryogenic gloves, quickly remove CLEVECORD enclosed in the metal canister(s). Immediately place the metal canister in a reservoir with LN2 or in the vapor phase of a LN2 freezer at a temperature at or below -150⁰C (if available).

f. Place all packing materials back inside the LN2 tank and replace the lid ensuring that the temperature probe extends to the bottom of the LN2 tank and that the temperature probe wire is not kinked.

g. Carefully open the metal canister with the canister opening tool (included). Handle with caution to avoid damage to CLEVECORD cryobag.

h. Inspect the integrity of the cryobag.

NOTE: If there is damage to the cryobag, return the cryobag to storage at or below -150°C (contain the cryobag in an overwrap if necessary). Consult with the transplant physician and contact Cleveland Cord Blood Center (CCBC).

i. Record the donor identification number (DIN) from the cryobag label on the Dry Shipper and HPC, Cord Blood Receipt Form. The DIN on CLEVECORD should include the CCBC Facility ID number (W4215). Large CLEVECORD products may be split into two cryobags, and the rotated flag characters after the DIN indicate the individual products, identified by flag codes 01 and 02.

j. Check that the CLEVECORD DIN agrees exactly with the DIN previously selected for the intended recipient. Verify the match and print and sign in Section 2, #11 on the Dry Shipper and HPC, Cord Blood Receipt Form.

k. Store CLEVECORD in a LN2 freezer until ready to thaw for use.

l. Complete section 2 of the Dry Shipper and HPC, Cord Blood Receipt Form and fax to Cleveland Cord Blood Center at (216) 896-0320.

m. Re-attach the provided padlock to the flat lid of the LN2 tank inside of the dry shipper and scramble the code for secured locking.

n. Secure the large rounded lid of the protective shipping container and follow instructions in Section VI. for return of the dry shipper.

NOTE: If there is any error or ambiguity with regard to the documentation or condition of the product, close the LN2 tank to keep the product at or below -150ºC. Immediately advise the staff of the Cleveland Cord Blood Center and the transplant physician. Do not proceed until the problem is resolved.

If documentation and product are acceptable, but your facility either has no LN2 freezer, or insufficient LN2 storage space for the frozen CLEVECORD product, the CCBC dry shipper can be used for temporary storage. Inform CCBC that return of the dry shipper will be delayed for purpose of temporary product storage on site.

If storage for more than 48 hours is required, add fresh LN2 to the tank inside the dry shipper to keep the product frozen until a completely satisfactory resolution for long-term storage and / or use of the frozen product has been reached. Confirm the temperature probe and data logger are properly installed as per step II.f, to ensure continued temperature monitoring.

III PREPARATION

a. Coordination with the clinical team

i. Confirm the transplant infusion time in advance, and adjust the start time for thaw so that the unit is available for infusion when the recipient is ready.

ii. Consult with the clinicians about final product volume based on the recipient’s weight and possible fluid restrictions to determine if the procedure for DMSO removal and volume reduction (Section VI.3) should be followed.

b. Prepare the water bath and verify that the temperature is 37°C ± 1°C.

c. Record the manufacturer information, lot number and expiration date (if applicable) of all reagents and disposables. Use only sterile materials when processing the CLEVECORD product.

d. Preparation of Dextran 40/Albumin solution.

NOTE: Use aseptic technique in a Biological Safety Cabinet for all processing steps, including all open-container processing and all spiking of container ports.

i. Combine 100 mL Dextran 40 solution and 100 mL 5% albumin solution in a sterile 300 mL transfer bag. Clamp the tubing with a hemostat. Prepare fresh solution on the day of transplant and store at 15-25°C.

ii. Fit one (1) 60 mL syringe with an 18 gauge needle and draw 25 mL Dextran-40/Albumin solution from the 300 mL transfer bag.

iii. Fit two (2) 60 mL syringes with 18 gauge needles and draw 60 mL Dextran-40/Albumin solution from the 300 mL transfer bag into each syringe.

e. Prepare a portable container with LN2 for storage of the frozen CLEVECORD product

f. With product and recipient files at hand, locate and remove the frozen product from storage in the LN2 freezer, or dry shipper, and verify product identity, labeling, accuracy of information, and container integrity. Two trained members of laboratory staff are required for this verification process.

g. Remove any segment attached to the unit, place into a 2 mL cryovial and store in either vapor or liquid phase of nitrogen (at or below -150°C).

h. Immediately transfer the product from LN2 storage into the portable LN2 container. Rest in vapor phase for 5-10 minutes prior to further manipulation.

IV PROCEDURE

Two different procedures for preparation of CLEVECORD for infusion are provided. The first procedure, referred to as the “Dilution” procedure is for dilution of thawed product, yielding ~170 mL product volume for infusion (Section IV.2 below). The second procedure, referred to as the “Dilution and Volume Reduction” procedure, involves centrifugation of thawed and diluted product, followed by supernatant removal, yielding a reduced (25-35 mL) product volume, amenable to infusion in pediatric patients (Section IV.3 below).

1. Thaw

a. Use cryoprotective gloves. Apply personal protective gear.

b. Open canister with the canister opening tool. Handle carefully to avoid damage to the cryobag containing the frozen CLEVECORD unit. Carefully examine the cryobag for breaks or cracks.

c. Remove the CLEVECORD cryobag from the canister.

d. Wipe the external surface of the cryobag with isopropyl alcohol.

e. Place the CLEVECORD cryobag into a clean plastic zip-lock bag. Let the air out of the zip-lock bag, and close it tightly. Use a sterile plastic zip-lock bag if available.

NOTE: Wiping the external surface of the cryobag with isopropyl alcohol before placing inside the sterile zip-lock bag reduces contamination risk and allows the thawing laboratory to potentially recover the product in the case of an unexpected leak or container failure during thawing, dilution and volume reduction procedures.

f. Place the plastic zip-lock bag containing the frozen CLEVECORD cryobag into the water bath pre-warmed at 37°C ± 1°C.

g. Document the start time of the thawing procedure.

h. Gently and carefully agitate the cryobag in the water bath to accelerate thawing and resuspension of the cells. Use your fingers to massage the bag to ensure uniform distribution of heat.

i. Watch closely for any cracks or breaks, as shown by red cells leaking from the cryobag into the plastic zip-lock bag.

j. If any leakage is seen, keep the leakage site upright to prevent further leaking while continuing to gently agitate the cryobag until the product is slushy. If feasible, point clamp the site of leakage with a hemostat. (See section VII EMERGENCY RECOVERY PROCEDURE IN THE EVENT OF A CONTAINER FAILURE for procedures for emergency recovery of the thawed cord blood cells).

k. If no leakage is seen, remove the plastic zip-lock bag from water bath when the product is completely slushy (i.e., when all visible ice-crystals have disappeared).

l. Document the stop time of the thawing procedure.

NOTE: The recommended expiration time of thawed CLEVECORD is 4 hours from the end time of thaw in step IV.1.1, if stored at 15-25°C.

m. Gently dry the outside of the bag, disinfect it with alcohol, and place it inside a Biological Safety Cabinet.

n. Proceed to either Section IV.2 for the Dilution procedure or Section IV.3 for the Dilution and Volume Reduction procedure.

2. Dilution (~170 mL volume for infusion)

a. Perform all steps in a Biological Safety Cabinet using aseptic technique

b. Obtain a Transplant Processing Two-Bag Set (See Figure 2).

c. Heat seal the tubing between Transplant and Transfer bags (between port on Infusion bag and SC-1). Discard the Transfer bag and connecting tubing.

d. Label the transplant bag with the CLEVECORD DIN and the name of the recipient, or according to institutional standard practice.

e. Confirm that all clamps are closed.

f. Remove the thawed CLEVECORD cryobag from the zip-lock bag. Using an iodine swab stick, disinfect the covers of both ports on the cryobag.

g. Disinfect scissors with alcohol and cut off the hermetically sealed covers to the spike ports on the cryobag.

h. Disinfect the cut surfaces of the two spike ports using an iodine swab stick and insert the two spikes of the transplant set.

i. Attach the 60 mL syringe with 25 mL Dextran-40/Albumin solution to female Luer lock. Open PC-1, PC-2 and PC-3 and then slowly add 25 mL of Dextran-40/Albumin solution to the thawed CLEVECORD product. Mix by gentle massage.

j. Close PC-3. Allow 5 minutes at 15-25°C for equilibration with the CLEVECORD cryobag and Transplant set placed flat on a clean surface.

k. Open PC-4. Transfer the diluted CLEVECORD from the cryobag to the Transplant bag. Close PC-1 and PC-2.

l. Attach the first syringe containing 60 mL Dextran-40/Albumin solution to the Luer lock. Open PC-1, PC-2, and PC-3. Transfer the 60 mL solution to the freezing bag. Close PC-3 and open PC-4. Transfer 60 mL Dextran-40/Albumin solution to the Transplant bag. Gently massage the Transplant bag in order to mix the CLEVECORD cell suspension.

m. Repeat step (l) using the second syringe containing 60 mL Dextran-40/Albumin solution. The final volume should approximate 170 mL (25 mL CLEVECORD unit and (25 + 60 + 60 =) 145 mL Dextran-40/Albumin solution).

n. Seal tubing between PC-4 and IP-1 and disconnect. Discard the spikes, Luer lock and connecting tubing.

o. Aseptically attach an 18 gauge needle to a 60 mL syringe, insert into port IP-1 and remove a 5 mL aliquot for quality control testing.

p. Place the Transplant bag inside a sterile overwrap bag and place flat inside a bin at ambient temperature (15-25°C).

q. Transport the CLEVECORD product to the clinical transplant site per the facility’s SOP.

NOTE: The recommended expiration time of thawed CLEVECORD is 4 hours from the end time of thaw, if stored at 15-25°C.

Figure 2: Transplant Processing Two-Bag Set

3. Dilution and Volume Reduction (~25-35 mL volume for infusion)

a. Perform all steps in a Biological Safety Cabinet using aseptic technique.

b. Obtain a Transplant Processing Two-Bag Set (See Figure 2).

c. Label both bags of the Two-Bag Set with the assigned CLEVECORD DIN.

d. Confirm that all clamps are closed.

e. Using an iodine swab stick, disinfect the covers of both ports on the thawed cryobag.

f. Disinfect scissors with alcohol and cut off the hermetically sealed covers to the spike ports on the thawed cryobag.

g. Disinfect the cut surfaces of the two spike ports using an iodine swab stick and insert the two spikes of the Two-Bag Set.

h. Attach Syringe 1 with 25 mL Dextran-40/Albumin solution to female Luer lock. Open PC-1, PC-2 and PC-3 and then slowly add 25 mL of Dextran-40/Albumin solution to the thawed CLEVECORD cryobag and mix.

i. Slowly and gently push and pull the syringe plunger to mix the CLEVECORD and Dextran-40/Albumin solutions; repeat three to four times.

j. Transfer the entire volume back into the cryobag. Close PC-3. Allow 5 minutes at 15-25°C for equilibration, with the CLEVECORD cryobag and Transplant set placed flat on a clean surface.

k. Open PC-4. Transfer the diluted CLEVECORD unit from the cryobag into the Transplant bag. Close PC-1 and PC-2.

l. Attach Syringe 2 containing 60 mL with Dextran-40/Albumin solution to the Luer lock. Open PC-3. Transfer the 60 mL solution via the cryobag into the diluted CLEVECORD in the Transplant bag. Gently massage the Transplant bag in order to mix the CLEVECORD cell suspension.

m. Repeat step (l.) using Syringe 3 containing 60 mL Dextran-40/Albumin solution. The final volume should now approximate 170 mL (25 mL CLEVECORD unit and (25 + 60 + 60 =) 145 mL Dextran-40/Albumin solution)

n. Close PC-3 and open PC-1 and PC-2. Pass the 170 mL diluted CLEVECORD suspension back and forth between the transplant bag and the cryobag two or three times to pass as many cells from the cryobag into the Transplant bag. Close PC-4.

o. Seal tubing between PC-4 and IP-1 and disconnect. Discard the spikes, Luer lock and connecting tubing.

p. Confirm PC-5 and SC-1 are closed. Place the Transplant Processing Two-Bag set in a sterile overwrap bag and in a centrifuge bucket.

q. Fully support the Transplant Processing Two-Bag set with thawed product with inserts to prevent formation of creases during centrifugation.

r. Balance carriers and centrifuge for 20 min at 400 x g at 10°C without brake.

s. After centrifugation, carefully remove the centrifuged Transplant Processing Two-Bag set from the centrifuge bucket. Be careful not to disturb the cells in the bottom of the bag. Record the date/time removed from the centrifuge.

t. Hang the Transplant Bag in a plasma extractor. Slowly close the door to the plasma extractor.

u. Open PC-5 and use SC-1 to adjust the flow of supernatant. Very slowly transfer most of the supernatant into the Transfer bag.

v. Empty the tubing between the bags by transferring air from the Transfer bag to Transplant Bag.

w. Close PC-5.

x. Aseptically attach an 18 gauge needle to a 60 mL syringe, insert into port IP-1 and remove a 5 mL aliquot for quality control testing.

y. Place the Transplant bag inside a sterile overwrap bag and place flat inside a bin at ambient temperature (15-25°C).

z. Transport the CLEVECORD product to the clinical transplant site per the facility’s SOP.

NOTE: The recommended expiration time of thawed CLEVECORD is 4 hours from the end time of thaw, if stored at 15-25°C.

V QUALITY CONTROL

Perform quality control assays per transplant center policies and procedures using the aliquot of thawed product obtained in step IV.2.o. or IV.3.x. Recommended assays include:

- Nucleated Cell count
- Viability test
- Viable CD34^+ cell count
- Colony Forming Unit
- Microbial cultures (aerobic, anaerobic and fungal)

VI ADMINISTRATIVE REQUIREMENTS

1. Prepare a written summary of the procedure, including:

a. CLEVECORD ID number

b. Date of receipt of CLEVECORD unit

c. Liquid nitrogen storage temperature

d. Date of thaw, including whether and at what stage leaks or cracks occurred

e. Date and time CLEVECORD unit removed from liquid nitrogen storage

f. Volume of final product

g. TNC (Total nucleated cell) count, CD34+ count

h. Viability of recovered cells (TNC or CD34+) plus name of test method used

i. Results of bacterial and fungal cultures

2. Make a copy of the report for your records

3. Fax a copy of the report to the Cleveland Cord Blood Center at (216) 896-0320

4. Return the dry shipper to the Cleveland Cord Blood Center. The return address is:

Cleveland Cord Blood Center
25001 Emery Road, Suite 150
Cleveland, OH 44128
Phone: (216) 896-0360
Fax: (216) 896-0320

VII EMERGENCY RECOVERY PROCEDURE IN THE EVENT OF A CONTAINER FAILURE

1. General Precautions

Use standard procedures and trained personnel to perform post-thaw sampling and/or bag rescue. As cryobags can be very fragile, handle the frozen cord blood bag with extreme care at every step including opening the metal containers, inspecting, thawing and/or washing. Perform all steps on lab benches, under biological safety cabinet, or another surface to prevent inadvertent drop of the frozen unit. To facilitate thawing, gradually remove the CLEVECORD unit from the liquid phase of the LN2 storage area, suspending in the vapor phase for at least five minutes prior to bringing the container to room temperature. Wipe the external surface of the cryobag with isopropyl alcohol before it is placed inside a sterile zip-lock bag. This will allow the cell laboratory to potentially recover the product in the case of an unexpected leak or container failure during thawing, dilution or volume reduction.

2. Emergency Recovery

a. If the CLEVECORD cryobag is observed to be cracked when removed from the LN2 storage container, or if cracks or leaks occur during thawing, immediately notify Cleveland Cord Blood Center by phone at (216) 378-3032 or (216) 896-0493. Notify the transplant physician and transplant team and the laboratory director as soon as possible.

b. The transplant physician or team will determine whether to use or discard the CLEVECORD product and whether any additional HPC, Cord Blood units should be requested.

c. If the transplant physician or team decides that the product in the leaking cryobag could be used, the CLEVECORD unit may be recovered as follows:

i. Obtain sterile sampling cups, sterile pipettes and syringes.

ii. Open a sterile sampling cup and set cup in working space to receive contents of zip-lock bag.

iii. If any contents remain within the broken CLEVECORD cryobag, remove the contents from the cryobag using sterile syringes.

iv. Wash all contents out of the CLEVECORD cryobag and transfer contents in a new transfer bag (Rescue Bag).

v. Using a sterile syringe, transfer 20 mL from the Dextran-40/Albumin solution in the 300 mL transfer bag into a sterile sample cup.

vi. Using a sterile pipette, obtain 3 mL of Dextran-40/Albumin solution from the sample cup and inject into the zip-lock bag containing the remaining CLEVECORD cryobag contents that leaked when thawing.

vii. Using a different sterile pipette, remove the CLEVECORD and Dextran-40/Albumin solution from the zip-lock bag and place in a sterile sample cup.

viii. Repeat steps vi and vii until all remaining CLEVECORD is transferred to the sterile sample cup.

ix. Using a sterile 20-mL syringe, draw the contents from the sterile sampling cup into the syringe. Inject the solution into the Rescue Bag.

x. Repeat until all of the contents from the sample cup are transferred into the Rescue Bag.

xi. Mix Rescue Bag well by inverting 180° for 10 to 15 times.

xii. Continue with Step k in Section IV.1.

Distributed by:

Cleveland Cord Blood Center
25001 Emery Road, Suite 150
Cleveland, OH 44128
License No. 2026

Principal Display Panel - Container

See attached documents

Volume approx.

25mL

Product: S1393000

Store at - 150°C or colder

Cryopreserved HPC, Cord Blood

Cleveland Cord Blood Center
25001 Emery Road Cleveland OH 44128
Label Version 7.0

Principal Display Panel - Carton

Properly Identify Intended Receipient and Product

A

Rh Positive

For Intravenous Administration

Do Not Irradiate

Do Not Use Leukoreduction Filter

Rx Only

HPC, CORD BLOOD

Cryopreserved

Approx 25ml;<5ml CPD

10% DMSO, 1% Dextran 40, 1% Hespen

Store at -150 C or colder

See package insert for full prescribing information and instructions for preparation.

Expiration

Date/Time

20 Apr 2022 23:59 EDT

(21 Apr, 2012 03:59 UTC)

Cleveland Cord Blood Center
25001 Emery Rd Cleveland OH
License #2026